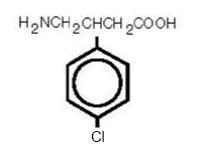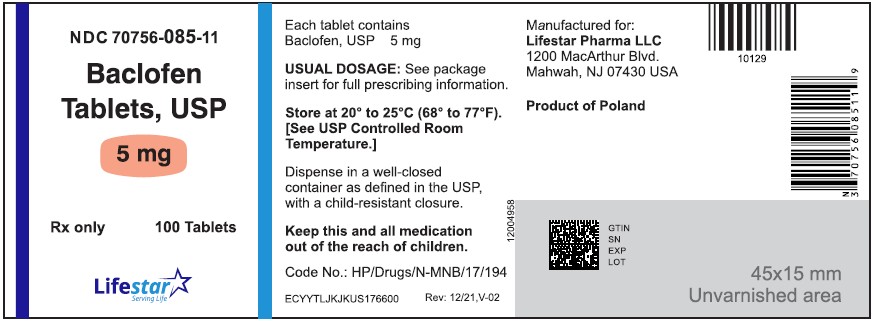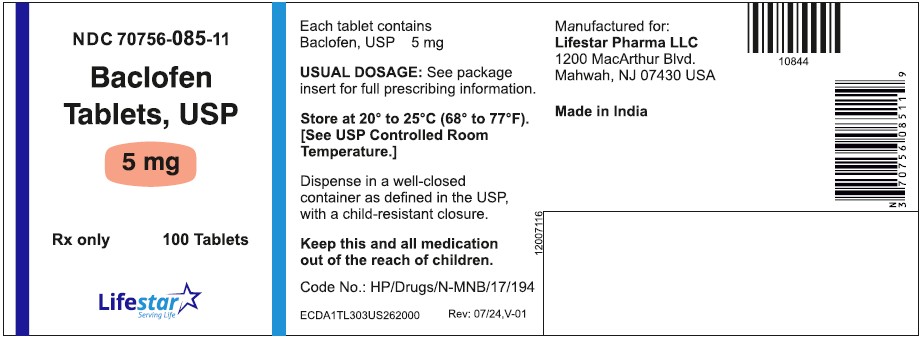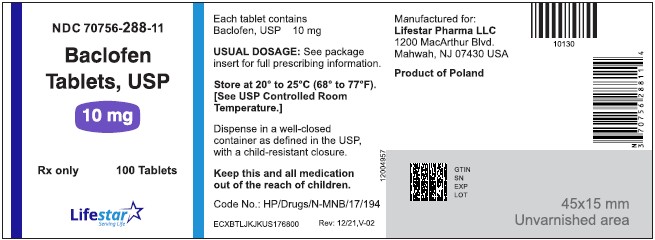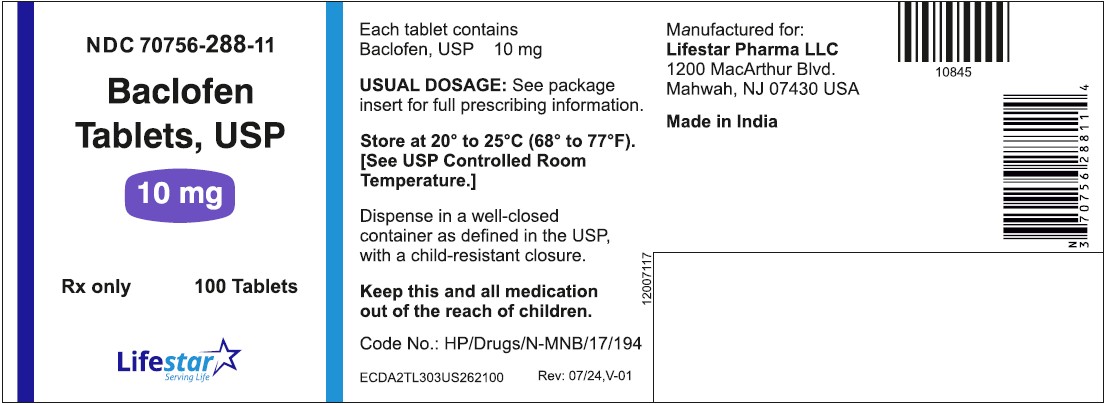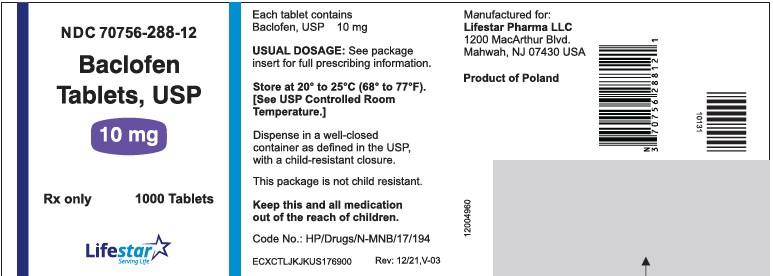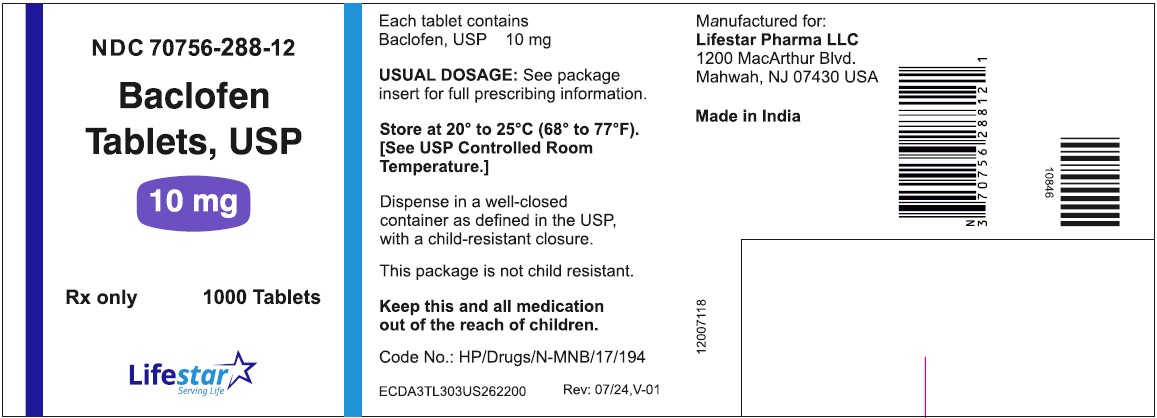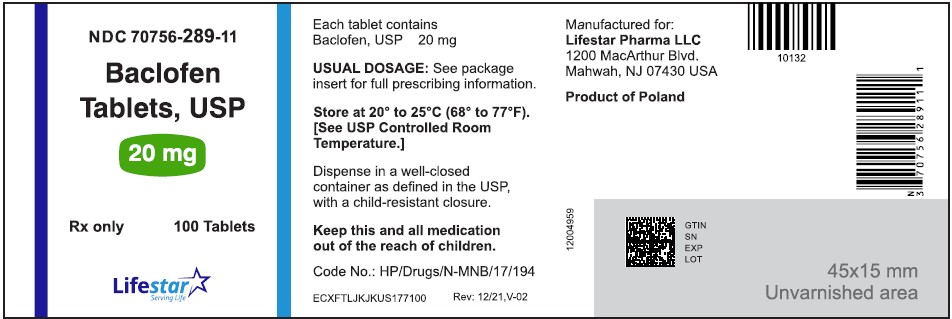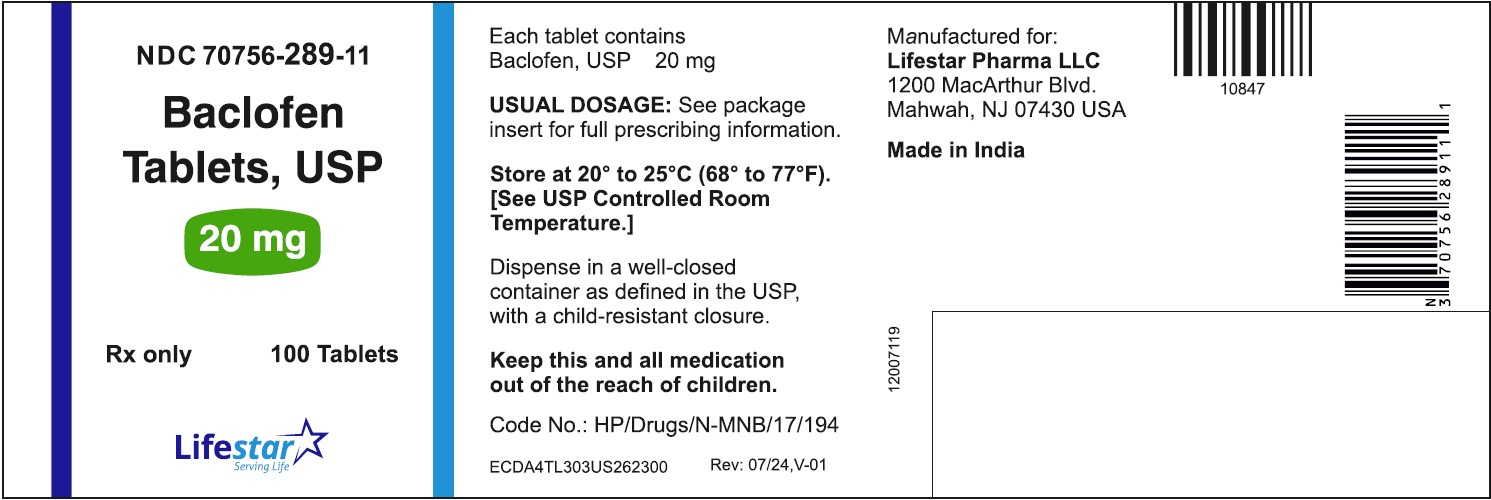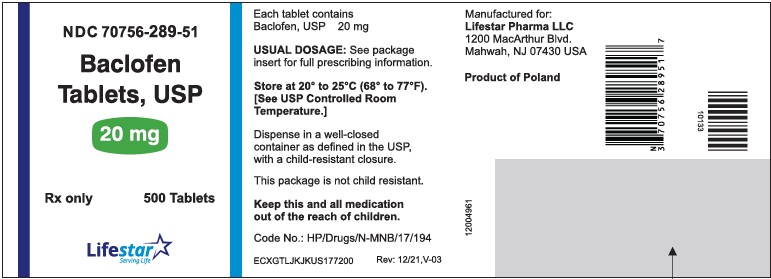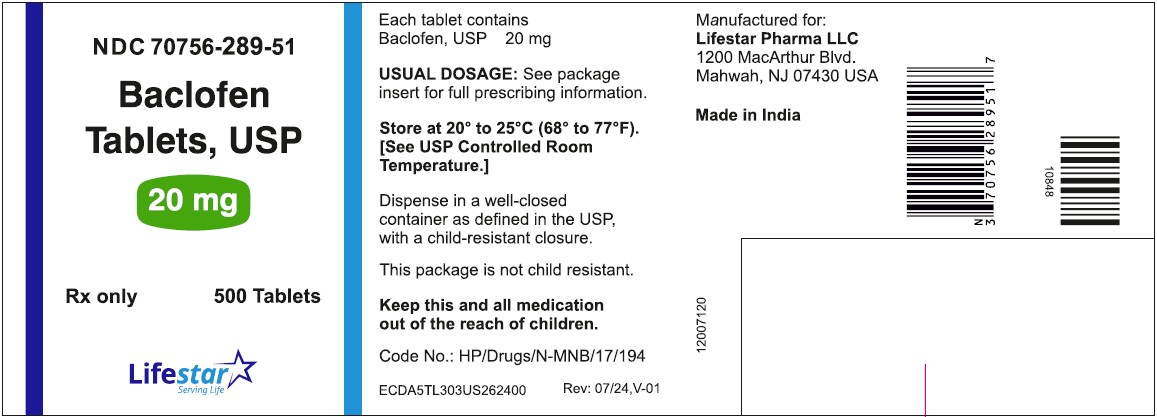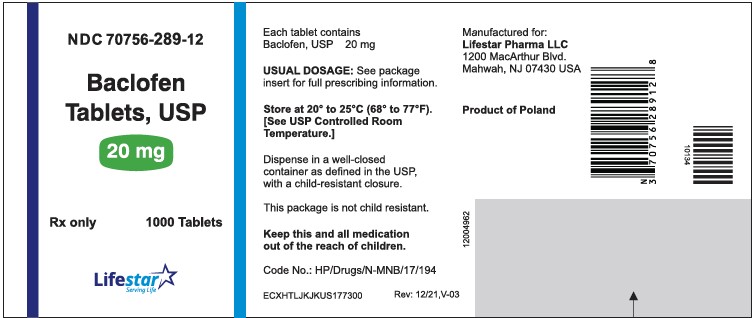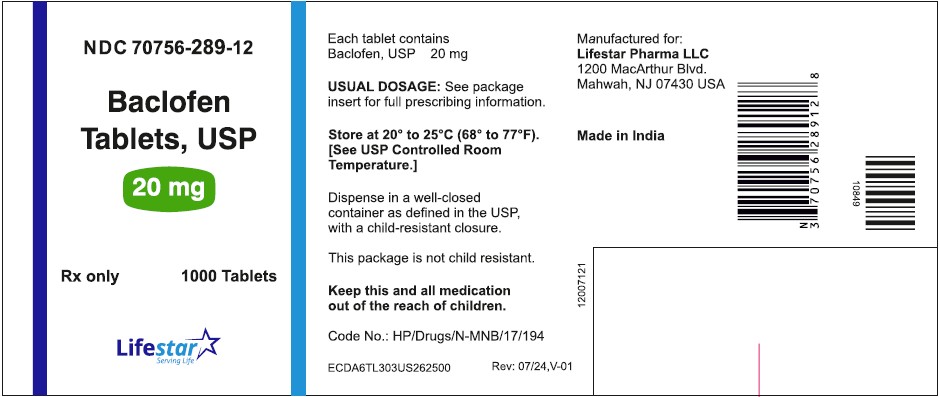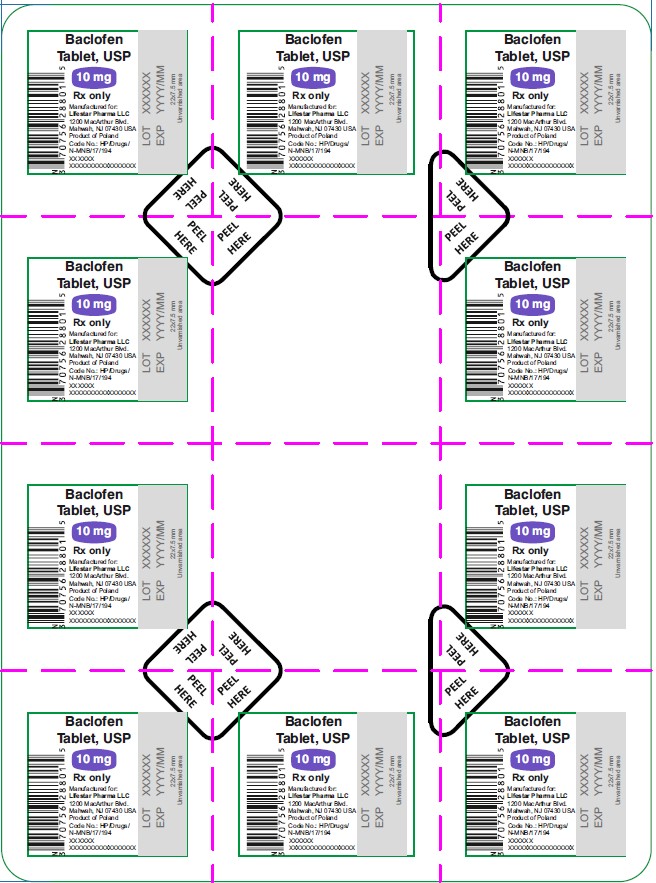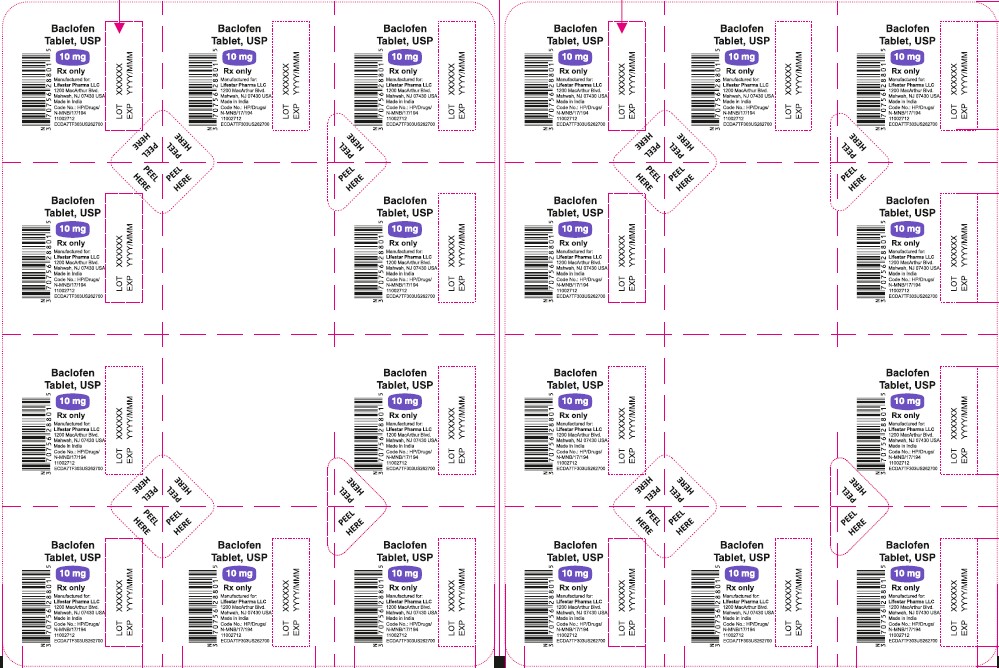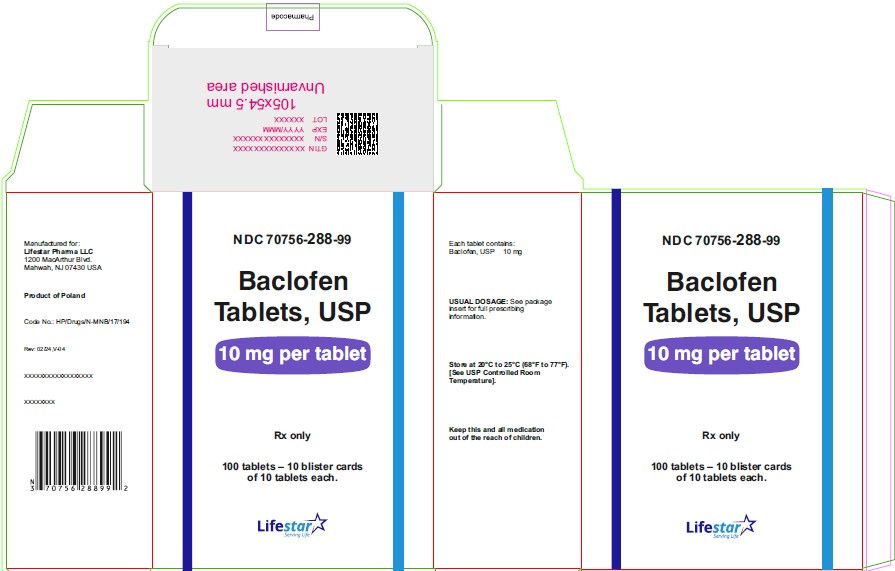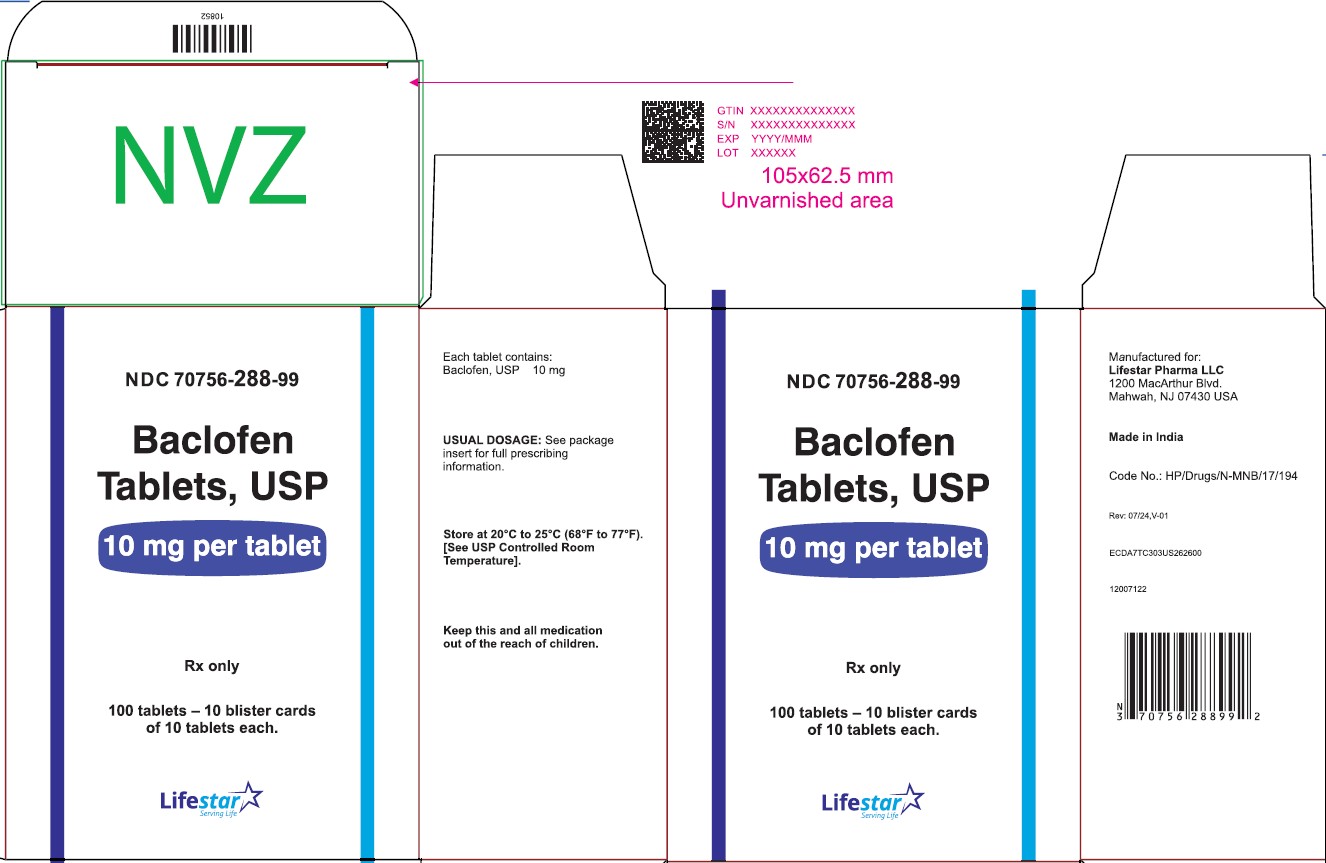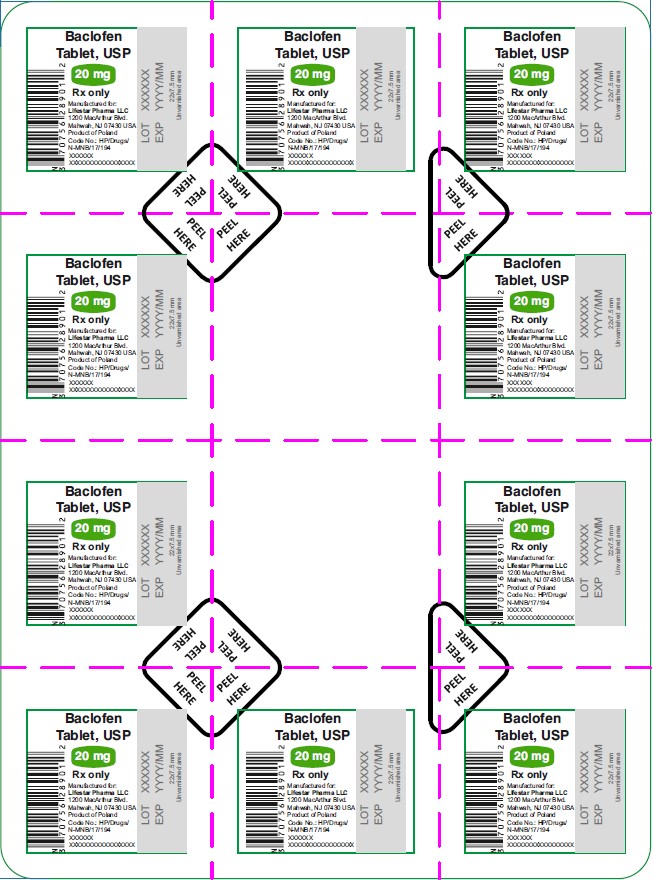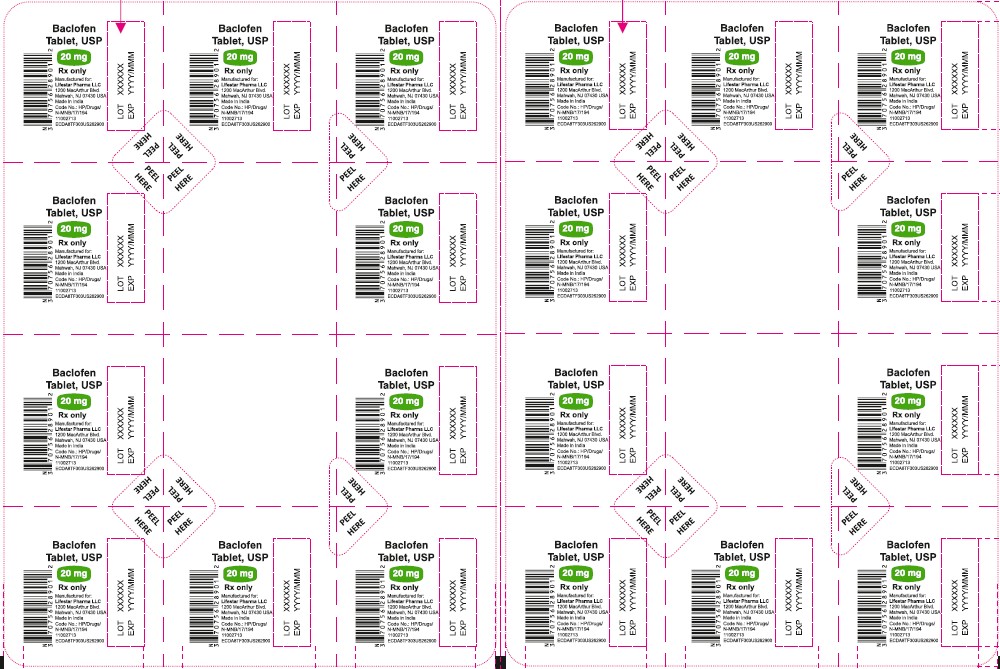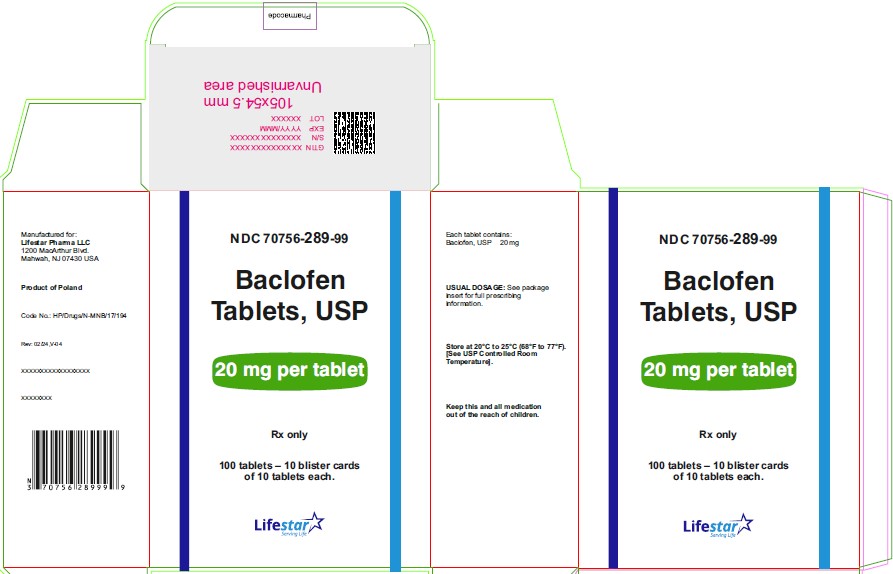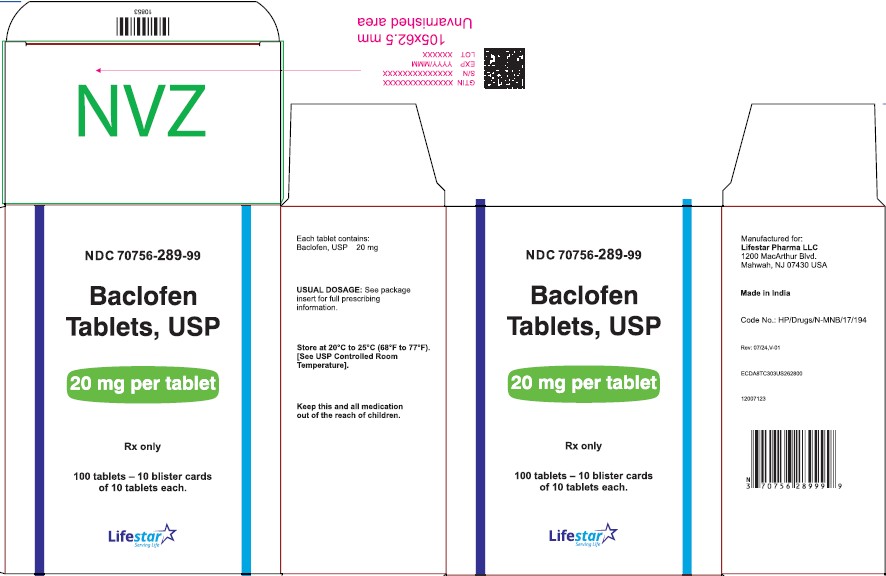 DRUG LABEL: Baclofen
NDC: 70756-085 | Form: TABLET
Manufacturer: Lifestar Pharma LLC
Category: prescription | Type: HUMAN PRESCRIPTION DRUG LABEL
Date: 20260227

ACTIVE INGREDIENTS: BACLOFEN 5 mg/1 1
INACTIVE INGREDIENTS: ANHYDROUS LACTOSE; CELLULOSE, MICROCRYSTALLINE; DIBASIC CALCIUM PHOSPHATE DIHYDRATE; MAGNESIUM STEARATE; SILICON DIOXIDE; SODIUM STARCH GLYCOLATE TYPE A

Baclofen Tablets, USP
Rx only

DESCRIPTION

Baclofen, USP is a muscle relaxant and antispastic.

Its chemical name is 4-amino-3-(4-chlorophenyl)-butanoic acid. The structural formula is:

C10H12ClNO2 M.W. 213.66

Baclofen, USP is a white to off-white odorless or practically odorless crystalline powder. It is slightly soluble in water, very slightly soluble in methanol and insoluble in chloroform.

Each tablet, for oral administration, contains 5 mg, 10 mg or 20 mg baclofen, USP. In addition, each tablet contains the following inactive ingredients: anhydrous lactose, colloidal silicon dioxide, dibasic calcium phosphate dihydrate, magnesium stearate, microcrystalline cellulose and sodium starch glycolate.

CLINICAL PHARMACOLOGY

The precise mechanism of action of baclofen is not fully known. Baclofen is capable of inhibiting both monosynaptic and polysynaptic reflexes at the spinal level, possibly by hyperpolarization of afferent terminals, although actions at supraspinal sites may also occur and contribute to its clinical effect. Although baclofen is an analog of the putative inhibitory neurotransmitter gamma-aminobutyric acid (GABA), there is no conclusive evidence that actions on GABA systems are involved in the production of its clinical effects. In studies with animals baclofen has been shown to have general CNS depressant properties as indicated by the production of sedation with tolerance, somnolence, ataxia, and respiratory and cardiovascular depression. Baclofen is rapidly and extensively absorbed and eliminated. Absorption may be dose-dependent, being reduced with increasing doses. Baclofen is excreted primarily by the kidney in unchanged form and there is relatively large intersubject variation in absorption and/or elimination.

INDICATIONS AND USAGE

Baclofen tablets are useful for the alleviation of signs and symptoms of spasticity resulting from multiple sclerosis, particularly for the relief of flexor spasms and concomitant pain, clonus, and muscular rigidity.

Patients should have reversible spasticity so that baclofen treatment will aid in restoring residual function. Baclofen tablets may also be of some value in patients with spinal cord injuries and other spinal cord diseases.

Baclofen tablets are not indicated in the treatment of skeletal muscle spasm resulting from rheumatic disorders.

The efficacy of baclofen in stroke, cerebral palsy, and Parkinson's disease has not been established and, therefore, it is not recommended for these conditions.

CONTRAINDICATIONS

Hypersensitivity to baclofen.

WARNINGS

a. Neonatal Withdrawal Symptoms: Withdrawal symptoms have been reported starting hours to days after delivery in neonates whose mothers were treated with oral baclofen throughout pregnancy. The symptoms of withdrawal in these infants have included increased muscle tone, tremor, jitteriness, and seizure. If the potential benefit justifies the potential risk to the fetus and oral baclofen is continued during pregnancy, gradually reduce the dose and discontinue baclofen before delivery. If slow withdrawal is not feasible, advise the parents or caregivers of the potential for neonatal withdrawal.

b. Abrupt Drug Withdrawal: Hallucinations and seizures have occurred on abrupt withdrawal of baclofen. Therefore, except for serious adverse reactions, the dose should be reduced slowly when the drug is discontinued.

c. Impaired Renal Function: Because baclofen is primarily excreted unchanged through the kidneys, it should be given with caution, and it may be necessary to reduce the dosage.

d. Stroke: Baclofen has not significantly benefited patients with stroke. These patients have also shown poor tolerability to the drug.

e. Pregnancy: Baclofen has been shown to increase the incidence of omphaloceles (ventral hernias) in fetuses of rats given approximately 13 times the maximum dose recommended for human use, at a dose which caused significant reductions in food intake and weight gain in dams. This abnormality was not seen in mice or rabbits.

There was also an increased incidence of incomplete sternebral ossification in fetuses of rats given approximately 13 times the maximum recommended human dose, and an increased incidence of unossified phalangeal nuclei of forelimbs and hindlimbs in fetuses of rabbits given approximately 7 times the maximum recommended human dose. In mice, no teratogenic effects were observed, although reductions in mean fetal weight with consequent delays in skeletal ossification were present when dams were given 17 and 34 times the human daily dose. There are no studies in pregnant women. Baclofen should be used during pregnancy only if the benefit clearly justifies the potential risk to the fetus.

PRECAUTIONS

Because of the possibility of sedation, patients should be cautioned regarding the operation of automobiles or other dangerous machinery, and activities made hazardous by decreased alertness. Patients should also be cautioned that the central nervous system effects of baclofen may be additive to those of alcohol and other CNS depressants.

Baclofen should be used with caution where spasticity is utilized to sustain upright posture and balance in locomotion or whenever spasticity is utilized to obtain increased function.

In patients with epilepsy, the clinical state and electroencephalogram should be monitored at regular intervals, since deterioration in seizure control and EEG have been reported occasionally in patients taking baclofen.

It is not known whether this drug is excreted in human milk. As a general rule, nursing should not be undertaken while a patient is on a drug since many drugs are excreted in human milk.

A dose-related increase in incidence of ovarian cysts and a less marked increase in enlarged and/or hemorrhagic adrenal glands was observed in female rats treated chronically with baclofen.

Ovarian cysts have been found by palpation in about 4% of the multiple sclerosis patients that were treated with baclofen for up to one year. In most cases these cysts disappeared spontaneously while patients continued to receive the drug. Ovarian cysts are estimated to occur spontaneously in approximately 1% to 5% of the normal female population.

Pediatric Use

Safety and effectiveness in pediatric patients below the age of 12 years have not been established.

ADVERSE REACTIONS

The most common is transient drowsiness (10 to 63%). In one controlled study of 175 patients, transient drowsiness was observed in 63% of those receiving baclofen compared to 36% of those in the placebo group. Other common adverse reactions are dizziness (5 to 15%), weakness (5 to 15%) and fatigue (2 to 4%).

Others reported:

Neuropsychiatric: Confusion (1 to 11%), headache (4 to 8%), insomnia (2 to 7%); and, rarely, euphoria, excitement, depression, hallucinations, paresthesia, muscle pain, tinnitus, slurred speech, coordination disorder, tremor, rigidity, dystonia, ataxia, blurred vision, nystagmus, strabismus, miosis, mydriasis, diplopia, dysarthria, epileptic seizure.

Cardiovascular: Hypotension (0 to 9%). Rare instances of dyspnea, palpitation, chest pain, syncope. Gastrointestinal: Nausea (4 to 12%), constipation (2 to 6%); and rarely, dry mouth, anorexia, taste disorder, abdominal pain, vomiting, diarrhea, and positive test for occult blood in stool.

Genitourinary: Urinary frequency (2 to 6%); and rarely, enuresis, urinary retention, dysuria, impotence, inability to ejaculate, nocturia, hematuria.

Other: Instances of rash, pruritus, ankle edema, excessive perspiration, weight gain, nasal congestion. Some of the CNS and genitourinary symptoms may be related to the underlying disease rather than to drug therapy. The following laboratory tests have been found to be abnormal in a few patients receiving baclofen: increased SGOT, elevated alkaline phosphatase, and elevation of blood sugar.

To report SUSPECTED ADVERSE REACTIONS, contact Lifestar Pharma LLC at 1-888-995-4337 or FDA at 1-800-FDA-1088 or www.fda.gov/medwatch.

OVERDOSAGE

Signs and Symptoms: Vomiting, muscular hypotonia, drowsiness, accommodation disorders, coma, respiratory depression and seizures.

Treatment: In the alert patient, empty the stomach promptly by induced emesis followed by lavage. In the obtunded patient, secure the airway with a cuffed endotracheal tube before beginning lavage (do not induce emesis). Maintain adequate respiratory exchange, do not use respiratory stimulants.

DOSAGE AND ADMINISTRATION

The determination of optimal dosage requires individual titration. Start therapy at a low dosage and increase gradually until optimum effect is achieved (usually between 40 to 80 mg daily).

The following dosage titration schedule is suggested:

5 mg t.i.d. for 3 days

10 mg t.i.d. for 3 days

15 mg t.i.d. for 3 days

20 mg t.i.d. for 3 days

Thereafter additional increases may be necessary but the total daily dose should not exceed a maximum of 80 mg daily (20 mg q.i.d.).

The lowest dose compatible with an optimal response is recommended. If benefits are not evident after a reasonable trial period, patients should be slowly withdrawn from the drug (see WARNINGS, Abrupt Drug Withdrawal).

HOW SUPPLIED

Baclofen Tablets USP, 5 mg are available as a white to off white, round, flat-faced, beveled edge tablet, debossed with "LS" on one side and "85" on the other side, containing 5 mg baclofen, USP are supplied as follows:

Bottle of 100 tablets, with child-resistant closure. NDC 70756-085-11

Baclofen Tablets USP, 10 mg are available as a white to off white, round, flat-faced, beveled edge tablet, debossed with "LS 288" on one side and functional scored on the other side, containing 10 mg baclofen, USP are supplied as follows:

Bottle of 100 tablets, with child-resistant closure. NDC 70756-288-11

Bottle of 1000 tablets. This package is not child resistant. NDC 70756-288-12

Unit-dose child-resistant blister pack of 100 (10 x 10) tablets. NDC 70756-288-99

NDC 70756-288-12 in bottle of 1000 tablets. This package is not child resistant.

Baclofen Tablets USP, 20 mg are available as a white to off white, round, flat-faced, beveled edge tablet debossed with "LS 289" on one side and functional scored on the other side, containing 20 mg baclofen, USP are supplied as follows:

Bottle of 100 tablets, with child-resistant closure. NDC 70756-289-11

Bottle of 500 tablets. This package is not child resistant. NDC 70756-289-51

Bottle of 1000 tablets. This package is not child resistant. NDC 70756-289-12

Unit-dose child-resistant blister pack of 100 (10 x 10) tablets. NDC 70756-289-99

Dispense in a well-closed container as defined in the USP, with a child-resistant closure.

Store at 20° to 25°C [68° to 77°F] [See USP Controlled Room Temperature].

KEEP THIS AND ALL MEDICATIONS OUT OF THE REACH OF CHILDREN.

Manufactured for:

Lifestar Pharma LLC

1200 MacArthur Blvd.

Mahwah, NJ 07430 USA

Product of Poland

or

Manufactured for:

Lifestar Pharma LLC

1200 MacArthur Blvd.

Mahwah, NJ 07430 USA

Made in India

Revised: October 2023, V-05

PACKAGE LABEL

NDC 70756-085-11

Baclofen

Tablets, USP

5 mg

Rx only

100 TABLETS

Product of Poland

NDC 70756-085-11

Baclofen

Tablets, USP

5 mg

Rx only

100 TABLETS

Made in India

PACKAGE LABEL

NDC 70756-288-11

Baclofen

Tablets, USP

10 mg

Rx only

100 TABLETS

Product of Poland

NDC 70756-288-11

Baclofen

Tablets, USP

10 mg

Rx only

100 TABLETS

Made in India

NDC 70756-288-12

Baclofen

Tablets, USP

10 mg

Rx only

1000 Tablets

Product of Poland

NDC 70756-288-12

Baclofen

Tablets, USP

10 mg

Rx only

1000 Tablets

Made in India

NDC 70756-289-11

Baclofen

Tablets, USP

20 mg

Rx only

100 Tablets

Product of Poland

NDC 70756-289-11

Baclofen

Tablets, USP

20 mg

Rx only

100 Tablets

Made in India

NDC 70756-289-51

Baclofen

Tablets, USP

20 mg

Rx only

500 Tablets

Product of Poland

NDC 70756-289-51

Baclofen

Tablets, USP

20 mg

Rx only

500 Tablets

Made in India

NDC 70756-289-12

Baclofen

Tablets, USP

20 mg

Rx only

1000 Tablets

Product of Poland

NDC 70756-289-12

Baclofen

Tablets, USP

20 mg

Rx only

1000 Tablets

Made in India

NDC 70756-288-01

Baclofen

Tablet, USP

10 mg

Rx only

10 tablets

Product of Poland

NDC 70756-288-01

Baclofen

Tablet, USP

10 mg

Rx only

10 tablets

Made in India

NDC 70756-288-99

Baclofen

Tablets, USP

10 mg per tablet

Rx only

100 Tablets

Product of Poland

NDC 70756-288-99

Baclofen

Tablets, USP

10 mg per tablet

Rx only

100 Tablets

Made in India

NDC 70756-289-01

Baclofen

Tablet, USP

20 mg

Rx only

10 Tablets

Product of Poland

NDC 70756-289-01

Baclofen

Tablet, USP

20 mg

Rx only

10 Tablets

Made in India

NDC 70756-289-99

Baclofen

Tablets, USP

20 mg per tablet

Rx only

100 Tablets

Product of Poland

NDC 70756-289-99

Baclofen

Tablets, USP

20 mg per tablet

Rx only

100 Tablets

Made in India